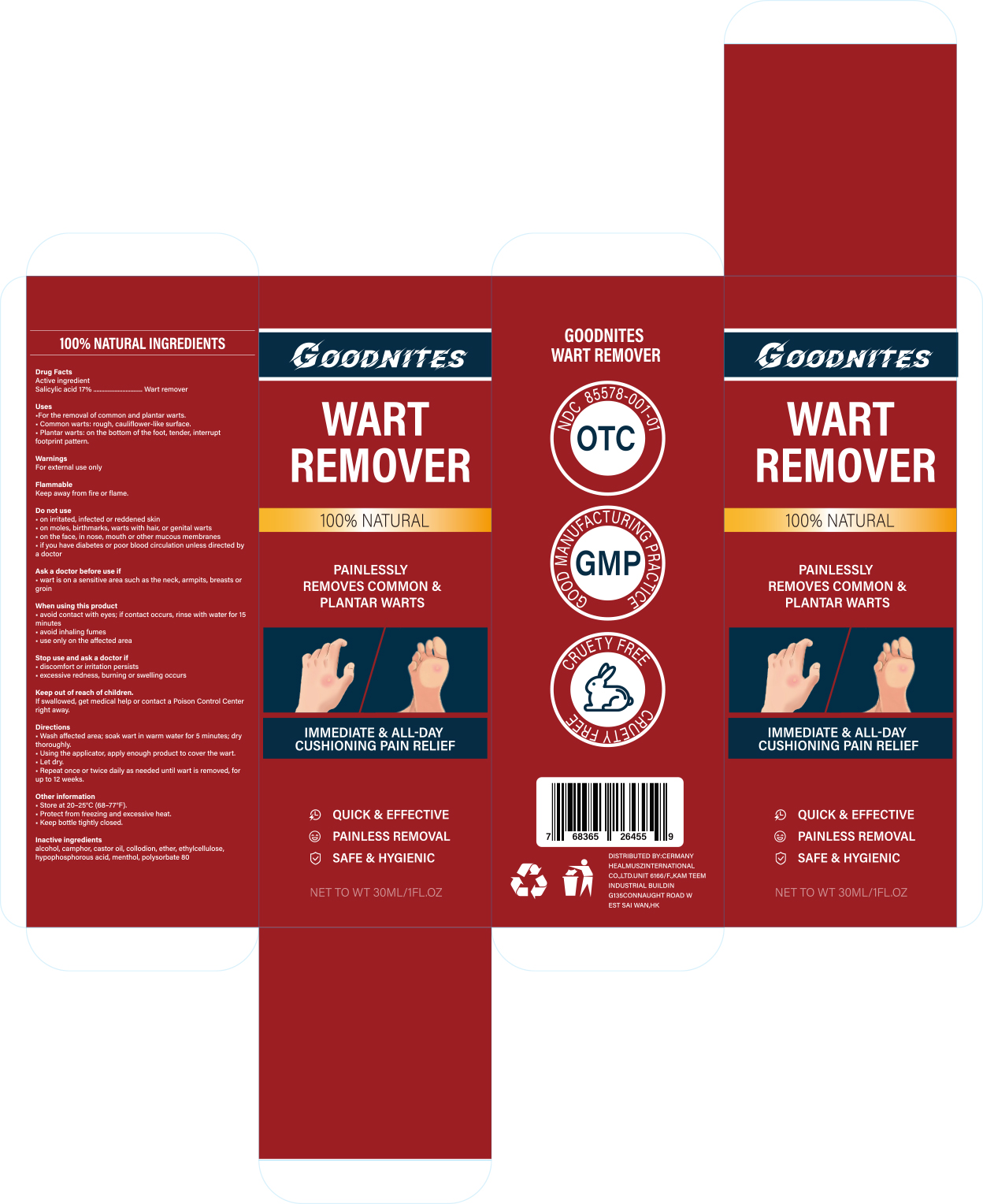 DRUG LABEL: Goodnites Wart Remover
NDC: 85578-001 | Form: LIQUID
Manufacturer: Zhengzhou Hangrui Network Technology Co., Ltd.
Category: otc | Type: HUMAN OTC DRUG LABEL
Date: 20251205

ACTIVE INGREDIENTS: SALICYLIC ACID 17 g/100 mL
INACTIVE INGREDIENTS: CAMPHOR (NATURAL); MENTHOL; CASTOR OIL; ALCOHOL; ETHER; POLYSORBATE 80; PYROXYLIN; ETHYLCELLULOSE, UNSPECIFIED; HYPOPHOSPHOROUS ACID

85578-001 Goodnites Wart Remover

ACTIVE INGREDIENT

Salicylic Acid

PURPOSE

Wart remover

INDICATIONS AND USAGE

For removing common warts and plantar warts.

WARNINGS

For external use only

When using this product, avoid contact witheyes. lf the product gets into your eyes, rinsewith water for 15 minutes. Avoid inhalingfumes. Close the cap tightly and store atroom temperature, away from heat sources

KEEP OUT OF REACH OF CHILDREN

If swallowed, get medical help or contact aPoison Control Center(1-800-222-1222)right away.

DOSAGE AND ADMINISTRATION

1. Clean and soften the affected
Area with warm water and dry it.
2.Apply the wart remover to each affected areausing the disposable applicator.Apply once in the morning and once in the
3.evening, daily.

INACTIVE INGREDIENT

alcohol, camphor, castor oil, collodion, ether, ethylcellulose, hypophosphorous acid, menthol, polysorbate 80